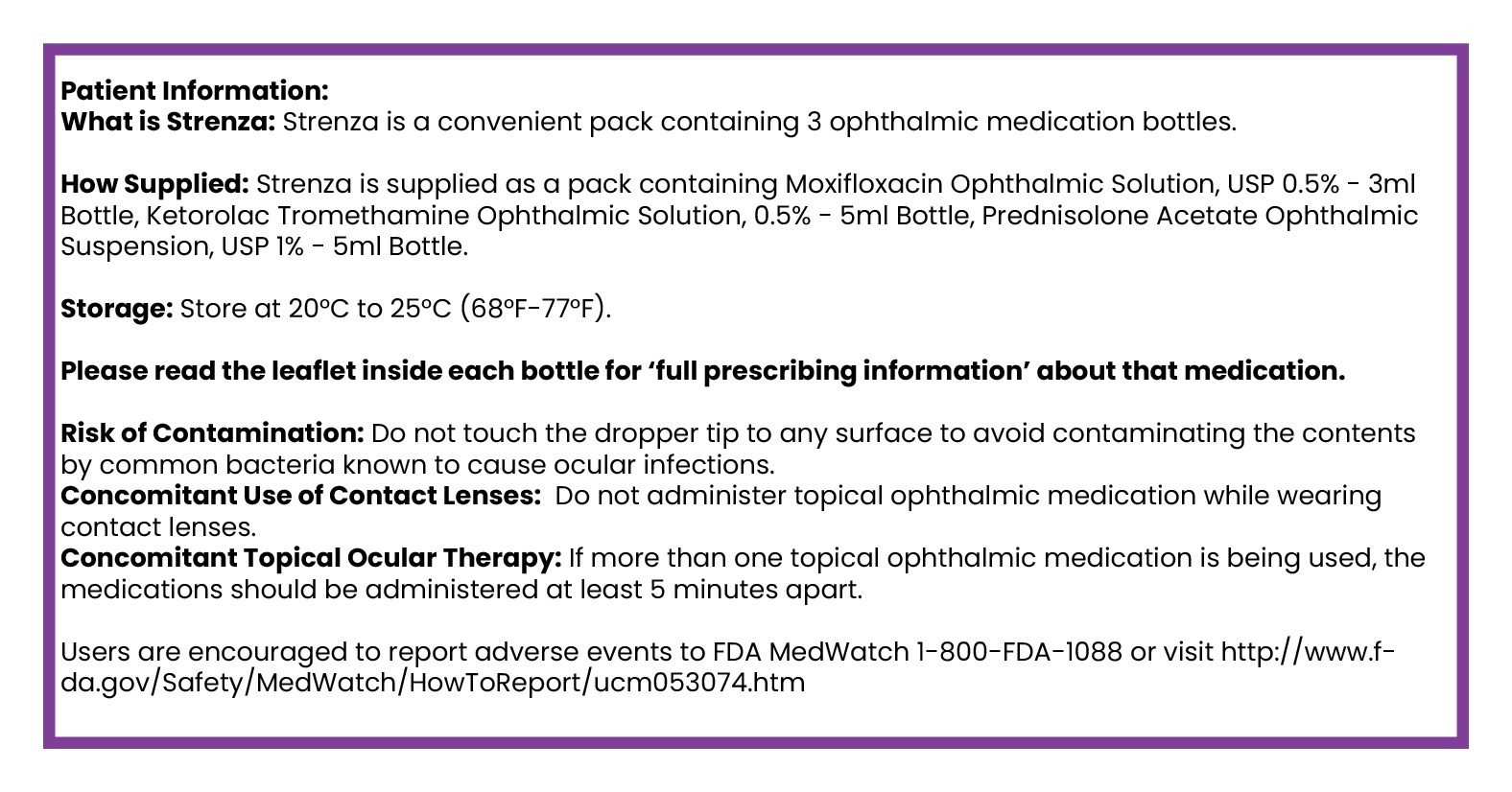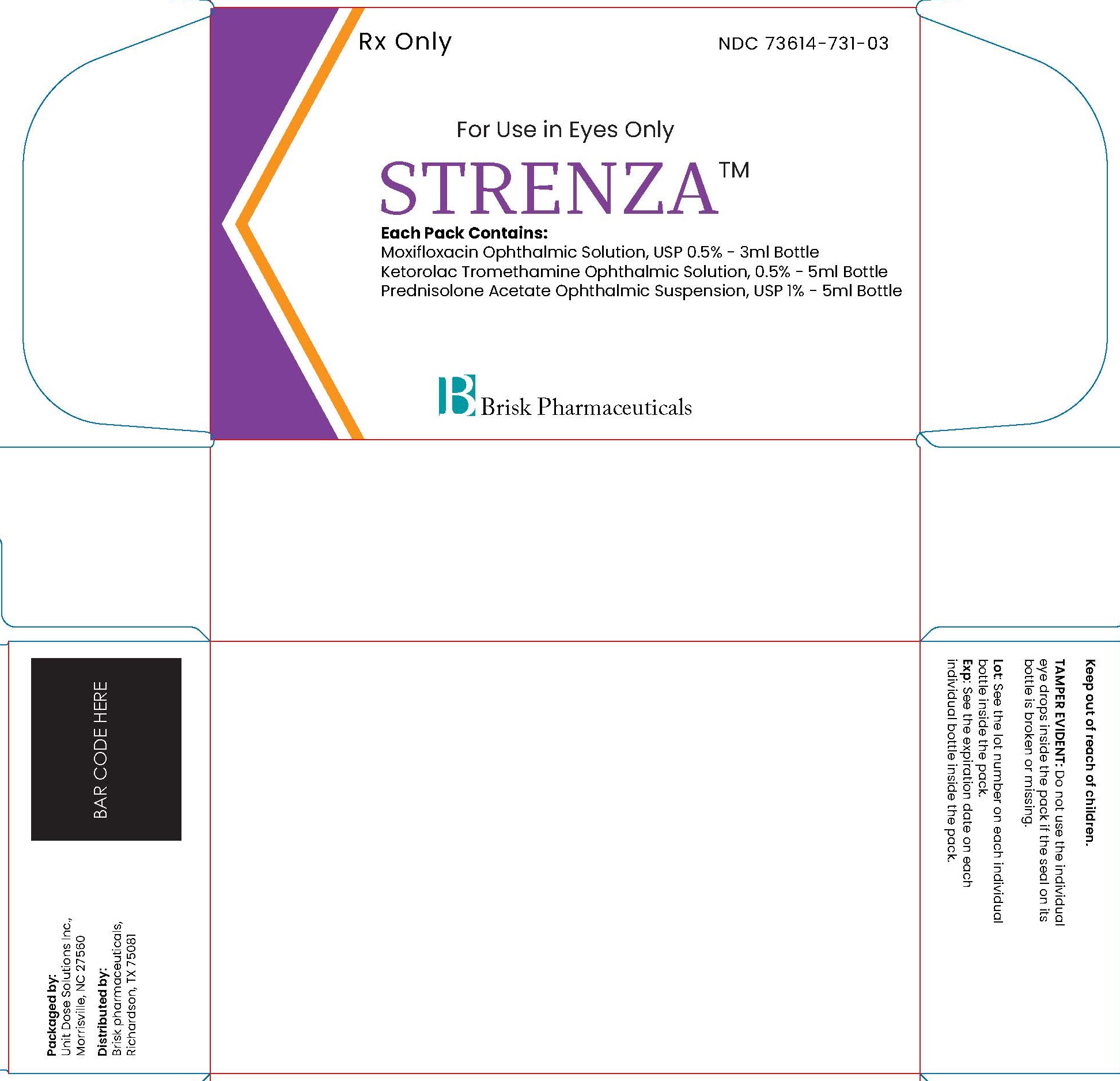 DRUG LABEL: STRENZA
NDC: 73614-731 | Form: KIT | Route: OPHTHALMIC
Manufacturer: Brisk Pharmaceuticals
Category: prescription | Type: HUMAN PRESCRIPTION DRUG LABEL
Date: 20241016

ACTIVE INGREDIENTS: KETOROLAC TROMETHAMINE 5 mg/1 mL; PREDNISOLONE ACETATE 10 mg/1 mL; MOXIFLOXACIN HYDROCHLORIDE MONOHYDRATE 5 mg/1 mL
INACTIVE INGREDIENTS: OCTOXYNOL-40; HYDROCHLORIC ACID; SODIUM HYDROXIDE; WATER; BENZALKONIUM CHLORIDE; EDETATE DISODIUM; SODIUM CHLORIDE; BENZALKONIUM CHLORIDE; POLYSORBATE 80; WATER; SODIUM HYDROXIDE; CITRIC ACID MONOHYDRATE; EDETATE DISODIUM; HYPROMELLOSE, UNSPECIFIED; SODIUM PHOSPHATE, DIBASIC, UNSPECIFIED FORM; GLYCERIN; BORIC ACID; HYDROCHLORIC ACID; SODIUM CHLORIDE; WATER; SODIUM HYDROXIDE

STRENZA

DESCRIPTION

Rx Only

NDC 73614-731-03

For Use in Eyes Only

STRENZA tm

Each Pack Contains:

Moxifloxacin Ophthalmic Solution, USP 0.5% - 3ml Bottle

Ketorolac Tromethamine Ophthalmic Solution, 0.5% - 5ml Bottle
Prednisolone Acetate Ophthalmic Suspension, USP 1% - 5ml Bottle

Brisk Pharmaceuticals

DESCRIPTION

Keep out of the reach of children.

TAMPER EVIDENT: Do not use the individual
eye drops inside the pack if the seal on its
bottle is broken or missing.

Lot: See the lot number on each individual
bottle inside the pack.
Exp: See the expiration date on each
individual bottle inside the pack.

Packaged by:
Unit Dose Solutions Inc.,
Morrisville, NC 27560
Distributed by:
Brisk pharmaceuticals,
Richardson, TX 75081